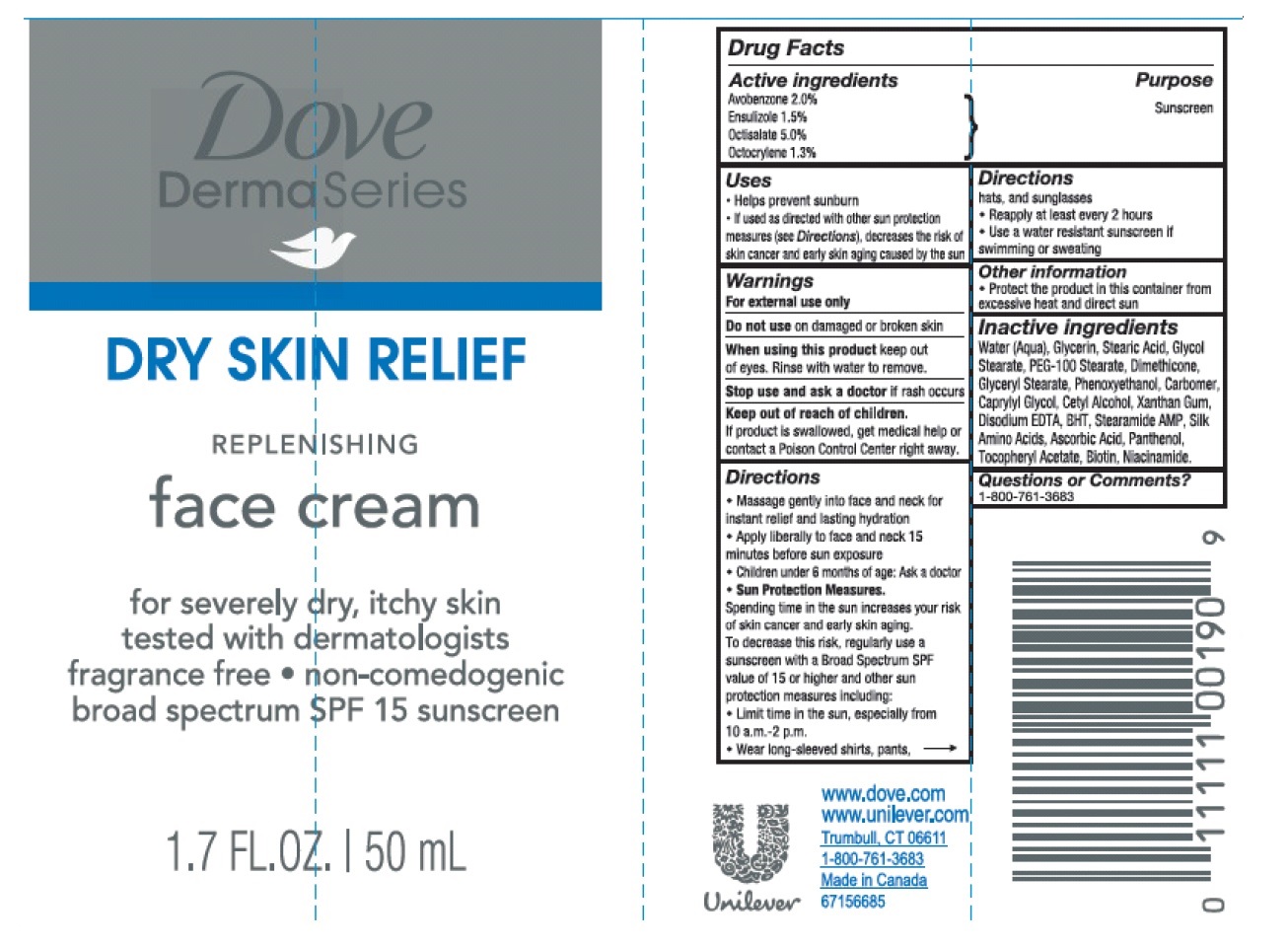 DRUG LABEL: Dove
NDC: 64942-1502 | Form: CREAM
Manufacturer: Conopco, Inc. d/b/a Unilever
Category: otc | Type: HUMAN OTC DRUG LABEL
Date: 20241024

ACTIVE INGREDIENTS: AVOBENZONE 2 g/100 mL; ENSULIZOLE 1.5 g/100 mL; OCTISALATE 5 g/100 mL; OCTOCRYLENE 1.3 g/100 mL
INACTIVE INGREDIENTS: WATER; GLYCERIN; STEARIC ACID; GLYCOL STEARATE; PEG-100 STEARATE; DIMETHICONE; GLYCERYL MONOSTEARATE; PHENOXYETHANOL; CARBOMER HOMOPOLYMER TYPE C (ALLYL PENTAERYTHRITOL CROSSLINKED); CAPRYLYL GLYCOL; CETYL ALCOHOL; XANTHAN GUM; EDETATE DISODIUM; BUTYLATED HYDROXYTOLUENE; STEARAMIDE AMP; AMINO ACIDS, SILK; ASCORBIC ACID; PANTHENOL; .ALPHA.-TOCOPHEROL ACETATE, D-; BIOTIN; NIACINAMIDE

Dove DermaSeries Dry Skin Relief Replenishing Face Cream SPF 15

Active ingredients

Avobenzone 2.0%

Ensulizole 1.5%

Octisalate 5.0%

Octocrylene 1.3%

Purpose

Sunscreen

Uses

- Helps prevent sunburn
- If used as directed with other sun protection measures (see Directions), decreases the risk of skin cancer and early skin aging caused by the sun

Warnings

For external use only

Do not use on damaged or broken skin

When using this product keep out of eyes. Rinse with water to remove.

Stop use and ask a doctor if rash occurs

Keep out of reach of children.

If product is swallowed, get medical help or contact a Poison Control Center right away.

Directions

- Massage gently into face and neck for instant relief and lasting hydration
- Apply liberally to face and neck 15 minutes before sun exposure
- Children under 6 months of age: Ask a doctor
- Sun Protection Measures.

Spending time in the sun increases your risk of skin cancer and early skin aging. To decrease this risk, regularly use a sunscreen with a Broad Spectrum SPF value of 15 or higher and other sun protection measures including:

- Limit time in the sun, especially from 10 a.m.-2 p.m.
- Wear long-sleeved shirts, pants, hats and sunglasses
- Reapply at least every 2 hours
- Use a water resistant sunscreen if swimming or sweating

Other information

- Protect the product in this container from excessive heat and direct sun

Inactive ingredients

Water (Aqua), Glycerin, Stearic Acid, Glycol Stearate, PEG-100 Stearate, Dimethicone, Glyceryl Stearate, Phenoxyethanol, Carbomer, Caprylyl Glycol, Cetyl Alcohol, Xanthan Gum, Disodium EDTA, BHT, Stearamide AMP, Silk Amino Acids, Ascorbic Acid, Panthenol, Tocopheryl Acetate, Biotin, Niacinamide.

Questions or Comments?

1-800-761-3683

For severely dry, itchy skin tested with dermatologists, fragrance free • non-comedogenic broad spectrum SPF 15 sunscreen